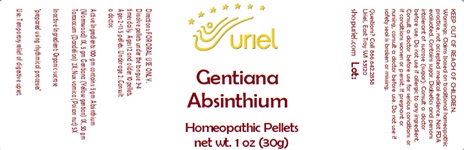 DRUG LABEL: Gentiana Absinthium
NDC: 48951-5008 | Form: PELLET
Manufacturer: Uriel Pharmacy Inc.
Category: homeopathic | Type: HUMAN OTC DRUG LABEL
Date: 20240409

ACTIVE INGREDIENTS: WORMWOOD 1 [hp_X]/1 1; GENTIANA LUTEA ROOT 1 [hp_X]/1 1; TARAXACUM PALUSTRE ROOT 2 [hp_X]/1 1; STRYCHNOS NUX-VOMICA SEED 5 [hp_X]/1 1
INACTIVE INGREDIENTS: SUCROSE

Gentiana Absinthium

INDICATIONS AND USAGE

Directions: FOR ORAL USE ONLY.

DOSAGE AND ADMINISTRATION

Dissolve pellets under the tongue 3-4 times daily. Ages 12 and older: 10 pellets. Ages 2-11: 5 pellets. Under age 2: Consult a doctor.

ACTIVE INGREDIENT

Active Ingredients: 100 gm contains: 5 gm Absinthium (Wormwood) 1X, 5 gm Gentiana (Yellow gentian) 1X, 50 gm Taraxacum (Dandelion) 2X; Nux vomica (Poison nut) 5X

Inactive Ingredient: Organic sucrose

"prepared using rhythmical processes"

PURPOSE

Use: Temporary relief of digestive upset.

KEEP OUT OF REACH OF CHILDREN.

WARNINGS

Warnings: Claims based on traditional homeopathic practice, not accepted medical evidence. Not FDA evaluated. Contains sugar. Diabetics and persons intolerant of sucrose (sugar): Consult a doctor before use. Do not use if allergic to any ingredient. Consult a doctor before use for serious conditions or if conditions worsen or persist. If pregnant or nursing, consult a doctor before use. Do not use if safety seal is broken or missing.

Questions? Call 866.642.2858
Uriel, East Troy, WI 53120
shopuriel.com Lot: